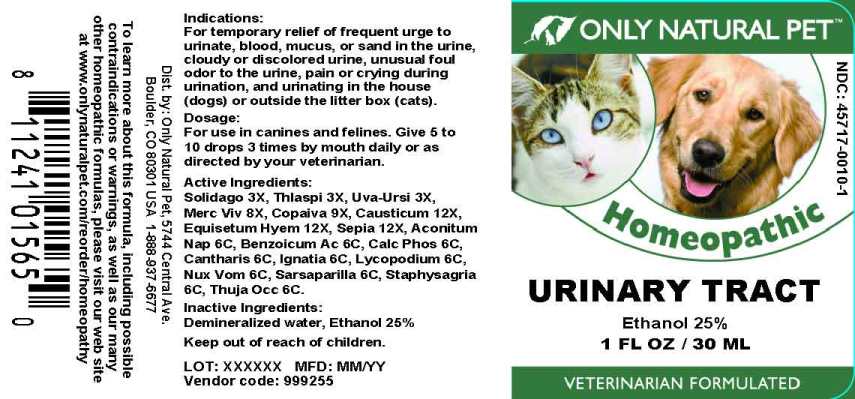 DRUG LABEL: Urinary Tract
NDC: 45717-0010 | Form: LIQUID
Manufacturer: Only Natural Pet Store
Category: homeopathic | Type: OTC ANIMAL DRUG LABEL
Date: 20241003

ACTIVE INGREDIENTS: SOLIDAGO VIRGAUREA FLOWERING TOP 3 [hp_X]/1 mL; CAPSELLA BURSA-PASTORIS 3 [hp_X]/1 mL; ARCTOSTAPHYLOS UVA-URSI LEAF 3 [hp_X]/1 mL; MERCURY 8 [hp_X]/1 mL; COPAIFERA OFFICINALIS RESIN 9 [hp_X]/1 mL; CAUSTICUM 12 [hp_X]/1 mL; EQUISETUM HYEMALE WHOLE 12 [hp_X]/1 mL; SEPIA OFFICINALIS JUICE 12 [hp_X]/1 mL; ACONITUM NAPELLUS WHOLE 6 [hp_C]/1 mL; BENZOIC ACID 6 [hp_C]/1 mL; TRIBASIC CALCIUM PHOSPHATE 6 [hp_C]/1 mL; LYTTA VESICATORIA 6 [hp_C]/1 mL; STRYCHNOS IGNATII SEED 6 [hp_C]/1 mL; LYCOPODIUM CLAVATUM SPORE 6 [hp_C]/1 mL; STRYCHNOS NUX-VOMICA SEED 6 [hp_C]/1 mL; SMILAX ORNATA ROOT 6 [hp_C]/1 mL; DELPHINIUM STAPHISAGRIA SEED 6 [hp_C]/1 mL; THUJA OCCIDENTALIS LEAFY TWIG 6 [hp_C]/1 mL
INACTIVE INGREDIENTS: WATER; ALCOHOL

Drug Facts:

ACTIVE INGREDIENTS:

Solidago Virgaurea 3X, Thlaspi Bursa-Pastoris 3X, Uva-Ursi 3X, Mercurius Vivus 8X, Copaiva Officinalis 9X, Causticum 12X, Equisetum Hyemale 12X, Sepia 12X, Aconitum Napellus 6C, Benzoicum Acidum 6C, Calcarea Phosphorica 6C, Cantharis 6C, Ignatia Amara 6C, Lycopodium Clavatum 6C, Nux Vomica 6C, Sarsaparilla (Smilax Regelii) 6C, Staphysagria 6C, Thuja Occidentalis 6C.

INDICATIONS:

For temporary relief of frequent urge to urinate, blood, mucus, or sand in the urine, cloudy or discolored urine, unusual foul odor to the urine, pain or crying during urination, and urinating in the house (dogs) or outside the litter box (cats).

WARNINGS:

To learn more about this formula, including possible contraindications or warnings, as well as our many other homeopathic formulas, please visit our web site at www.onlynaturalpet.com/reorder/homeopathy

KEEP OUT OF REACH OF CHILDREN:

DIRECTIONS:

For use in canines and felines. Give 5 to 10 drops 3 times by mouth daily or as directed by your veterinarian.

INDICATIONS:

For temporary relief of frequent urge to urinate, blood, mucus, or sand in the urine, cloudy or discolored urine, unusual foul odor to the urine, pain or crying during urination, and urinating in the house (dogs) or outside the litter box (cats).

INACTIVE INGREDIENTS:

Demineralized water, Ethanol 25%

QUESTIONS:

Dist. by: Only Natural Pet, 5744 Central Ave.

Boulder, CO 80301 USA 1-888-937-6677

PACKAGE LABEL DISPLAY:

ONLY NATURAL PET

NDC : 45717-0010-1

Homeopathic

URINARY TRACT

1 FL OZ / 30ML